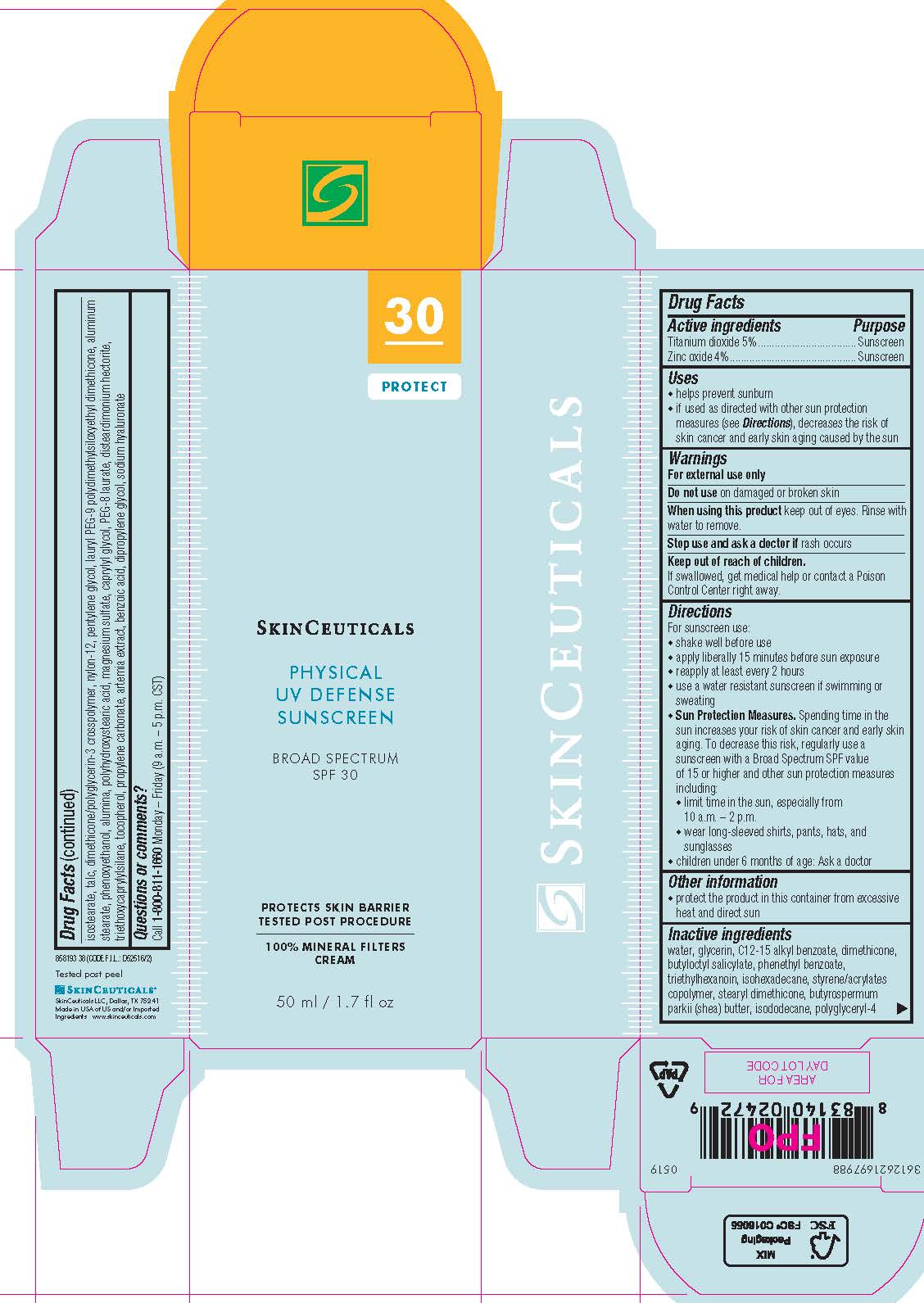 DRUG LABEL: SkinCeuticals Physical UV Defense Broad Spectrum SPF 30 Sunscreen
NDC: 49967-472 | Form: CREAM
Manufacturer: L'Oreal USA Products Inc
Category: otc | Type: HUMAN OTC DRUG LABEL
Date: 20241230

ACTIVE INGREDIENTS: TITANIUM DIOXIDE 50 mg/1 mL; ZINC OXIDE 40 mg/1 mL
INACTIVE INGREDIENTS: WATER; GLYCERIN; ALKYL (C12-15) BENZOATE; DIMETHICONE; BUTYLOCTYL SALICYLATE; PHENETHYL BENZOATE; TRIETHYLHEXANOIN; ISOHEXADECANE; STYRENE/ACRYLAMIDE COPOLYMER (500000 MW); STEARYL TRISILOXANE; SHEA BUTTER; ISODODECANE; POLYGLYCERYL-4 ISOSTEARATE; TALC; NYLON-12; PENTYLENE GLYCOL; LAURYL PEG-9 POLYDIMETHYLSILOXYETHYL DIMETHICONE; ALUMINUM STEARATE; PHENOXYETHANOL; ALUMINUM OXIDE; POLYHYDROXYSTEARIC ACID (2300 MW); MAGNESIUM SULFATE, UNSPECIFIED FORM; CAPRYLYL GLYCOL; PEG-8 LAURATE; DISTEARDIMONIUM HECTORITE; TRIETHOXYCAPRYLYLSILANE; TOCOPHEROL; PROPYLENE CARBONATE; ARNICA MONTANA; BENZOIC ACID; DIPROPYLENE GLYCOL; HYALURONATE SODIUM

Drug Facts

Active ingredients

Titanium dioxide 5%

Zinc oxide 4%

Purpose

Sunscreen

Uses

- helps prevent sunburn

- if used as directed with other sun protection measures (see Directions), decreases the risk of skin cancer and early skin aging caused by the sun

Warnings

For external use only

Do not use

on damaged or broken skin

When using this product

keep out of eyes. Rinse with water to remove.

Stop use and ask a doctor if

rash occurs

Keep out of reach of children.

If swallowed, get medical help or contact a Poison Control Center right away.

Directions

● shake well before use

● apply liberally 15 minutes before sun exposure

● reapply at least every 2 hours

● use a water resistant sunscreen if swimming or sweating

● Sun Protection Measures. Spending time in the sun increases your risk of skin cancer and early skin aging. To decrease this risk,

regularly use a sunscreen with a Broad Spectrum SPF value of 15 or higher and other sun protection measures including:

● limit time in the sun, especially from 10 a.m. – 2 p.m.

● wear long-sleeved shirts, pants, hats, and sunglasses

● children under 6 months of age: Ask a doctor

Other information

protect the product in this container from excessive heat and direct sun

Inactive ingredients

water, glycerin, c12-15 alkyl benzoate, dimethicone, butyloctyl salicylate, phenethyl benzoate, triethylhexanoin, isohexadecane, styrene/acrylates copolymer, stearyl dimethicone, butyrospermum parkii (shea) butter, isododecane, polyglyceryl-4 isostearate, talc, dimethicone/polyglycerin-3 crosspolymer, nylon-12, pentylene glycol, lauryl PEG-9 polydimethylsiloxyethyl dimethicone, aluminum stearate, phenoxyethanol, alumina, polyhydroxystearic acid, magnesium sulfate, caprylyl glycol, PEG-8 laurate, disteardimonium hectorite, triethoxycaprylylsilane, tocopherol, propylene carbonate, artemia extract, benzoic acid, dipropylene glycol, sodium hyaluronate

Questions or comments?

Call 1-800-811-1660

Monday - Friday (9 a.m. - 5 p.m. CST)